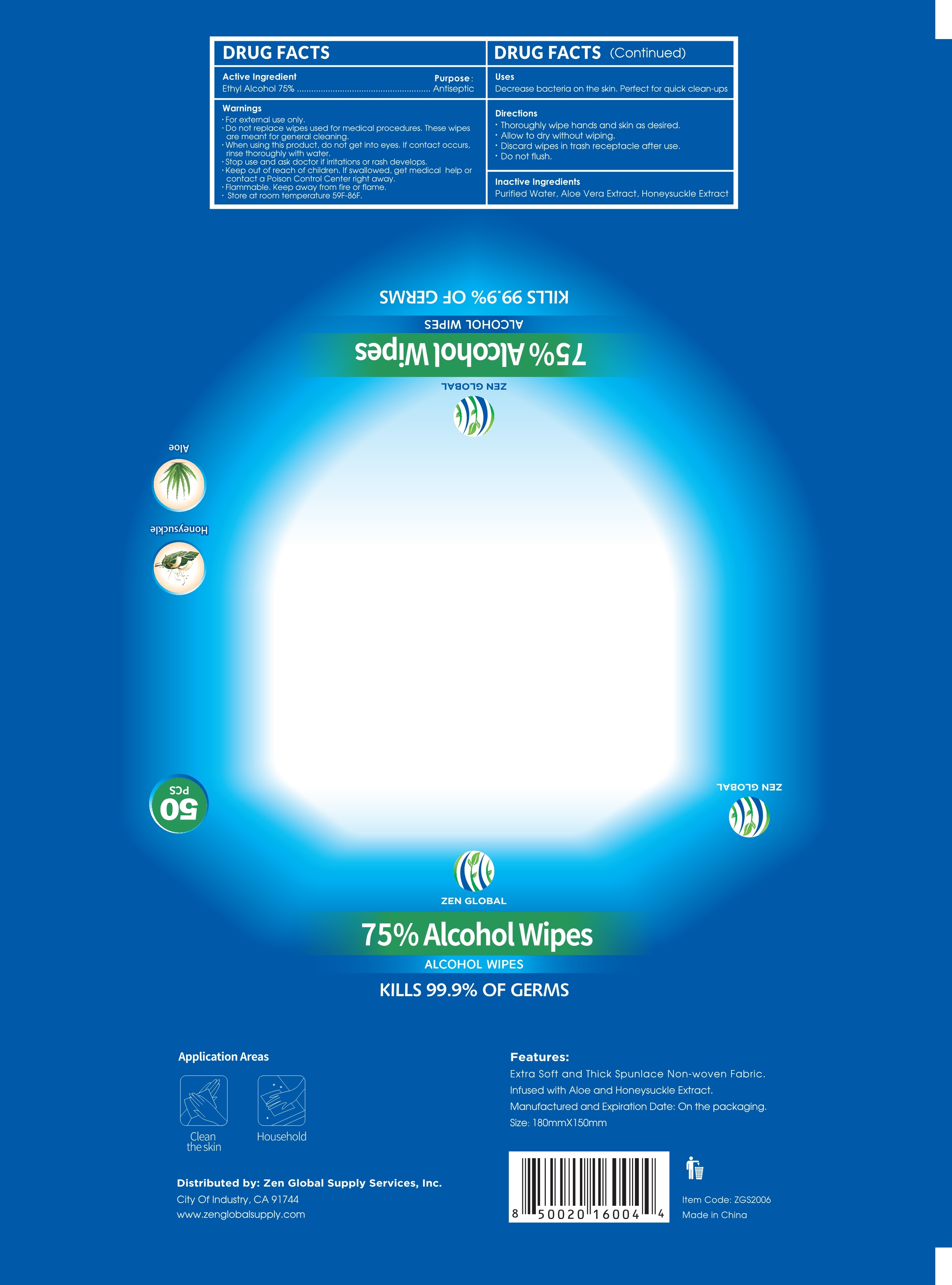 DRUG LABEL: 75% Alcohol wipes
NDC: 42129-010 | Form: CLOTH
Manufacturer: Fustin(Xiamen) Commodity Co., ltd
Category: otc | Type: HUMAN OTC DRUG LABEL
Date: 20200716

ACTIVE INGREDIENTS: ALCOHOL 75 1/100 1
INACTIVE INGREDIENTS: ALOE VERA LEAF; LONICERA DASYSTYLA WHOLE; WATER

75% Alcohol wipes

Active Ingredient(s)

Ethyl Alcohol 75%

Purpose

Antiseptic

Warnings

For external use only.
Flammable. Keep away from fire or flame.
Store at room temperature 59F-86F

INDICATIONS AND USAGE

Decrease bacteria on the skin. Perfect for quick clean-ups

Do not use

Do not replace wipes used for medical procedures. These wipes are meant for general cleaning

Stop use and ask doctor if irritations or rash develops.

Keep out of reach of children. If swallowed, get medical help or contact a Poison Control Center right away.

Directions

Thoroughly wipe hands and skin as desired
Allow to dry without wiping
Discard wipes in trash receptacle after use
Do not flush

Inactive ingredients

Purified Water, Aloe Vera Extract, Honeysuckle Extract